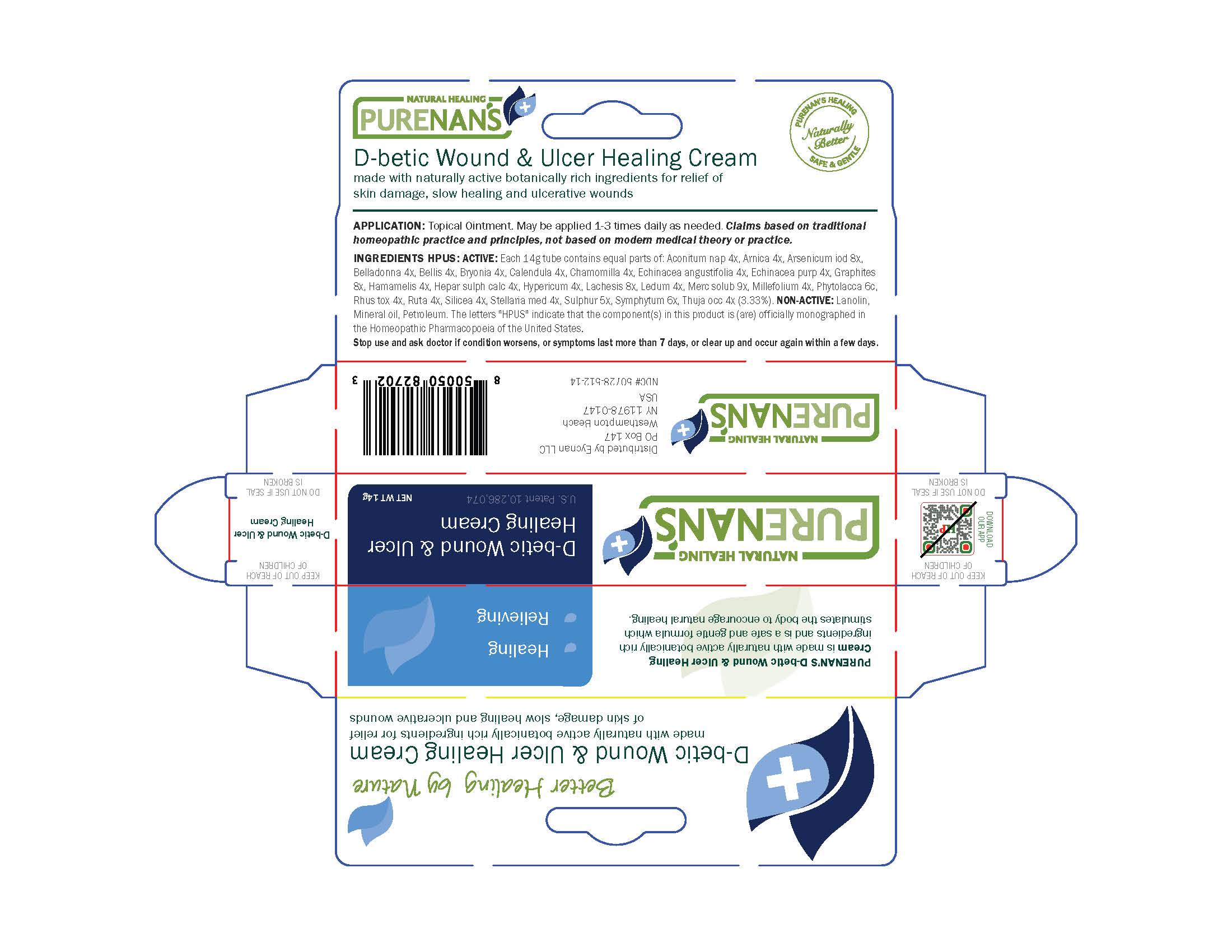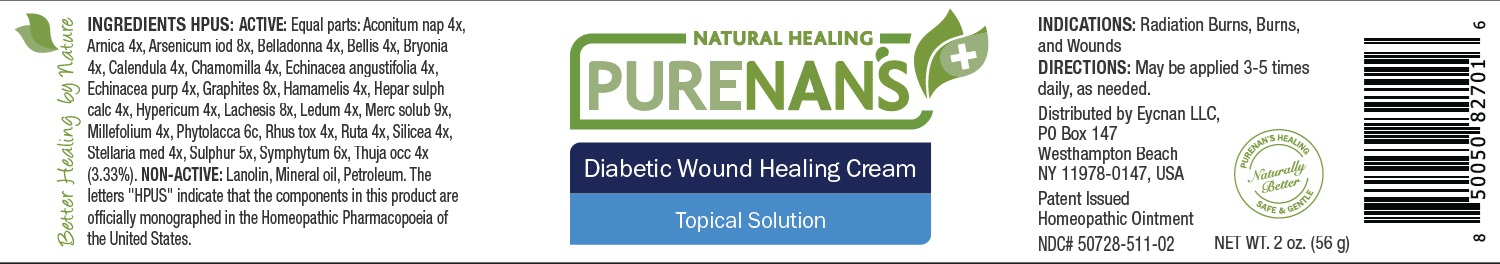 DRUG LABEL: Purenans Healing
NDC: 50728-511 | Form: OINTMENT
Manufacturer: Eycnan, LLC
Category: homeopathic | Type: HUMAN OTC DRUG LABEL
Date: 20241004

ACTIVE INGREDIENTS: ACONITUM NAPELLUS 4 [hp_X]/57 g; ARNICA MONTANA 4 [hp_X]/57 g; ARSENIC TRIIODIDE 8 [hp_X]/57 g; ATROPA BELLADONNA 4 [hp_X]/57 g; BELLIS PERENNIS 4 [hp_X]/57 g; BRYONIA ALBA ROOT 4 [hp_X]/57 g; CALENDULA OFFICINALIS FLOWERING TOP 4 [hp_X]/57 g; MATRICARIA RECUTITA 4 [hp_X]/57 g; ECHINACEA ANGUSTIFOLIA 4 [hp_X]/57 g; ECHINACEA PURPUREA 4 [hp_X]/57 g; GRAPHITE 8 [hp_X]/57 g; HAMAMELIS VIRGINIANA ROOT BARK/STEM BARK 4 [hp_X]/57 g; CALCIUM SULFIDE 4 [hp_X]/57 g; HYPERICUM PERFORATUM 4 [hp_X]/57 g; LACHESIS MUTA VENOM 8 [hp_X]/57 g; LEDUM PALUSTRE TWIG 4 [hp_X]/57 g; ACHILLEA MILLEFOLIUM 4 [hp_X]/57 g; MERCURIUS SOLUBILIS 9 [hp_X]/57 g; PHYTOLACCA AMERICANA ROOT 6 [hp_C]/57 g; RUTA GRAVEOLENS FLOWERING TOP 4 [hp_X]/57 g; TOXICODENDRON PUBESCENS LEAF 4 [hp_X]/57 g; SILICON DIOXIDE 4 [hp_X]/57 g; STELLARIA MEDIA 4 [hp_X]/57 g; SULFUR 5 [hp_X]/57 g; COMFREY ROOT 6 [hp_X]/57 g; THUJA OCCIDENTALIS LEAFY TWIG 4 [hp_X]/57 g
INACTIVE INGREDIENTS: LANOLIN; PETROLATUM; MINERAL OIL

Purenans Healing Cream

PURPOSE

Purenans Healing Cream

Topical Solution

INDICATIONS AND USAGE

Promotes and support healing of wounds, cuts and burns

General anti-infective wound healing cream

Diabetic ulcers

May reduce healing time for persistent wounds

ACTIVE INGREDIENT

Aconitum nap 4x, Arnica 4x, Arsenicum iod 8x, Belladonna 4x, Bellis 4x, Bryonia 4x, Calendula 4x, Chamomilla 4x, Echinacea angustifolia 4x, Echinacea purp 4x, Graphites 8x, Hamamelis 4x, Hepar sulph cacl 4x, Hypericum 4x, Lachesis 8x, Ledum 4x, Merc solub 9x, Millefolium 4x, Phytolacca 6c, Rhus tox 4x, Ruta 4x, Silicea 4x, Stellaria med 4x, Sulphur 5x, Symphytum 6x, Thuja occ 4x.

INACTIVE INGREDIENT

Lanolin, Petroleum, Mineral Oil

DOSAGE AND ADMINISTRATION

May be applied 3-5 times daily, as needed.

Warning

For external use only. Do not use if you are allergic to any of this products ingredients.

Keep ouf of reach of children

Warning

Keep out of reach of children

PACKAGE LABEL

Add image transcription here...

Add image transcription here...